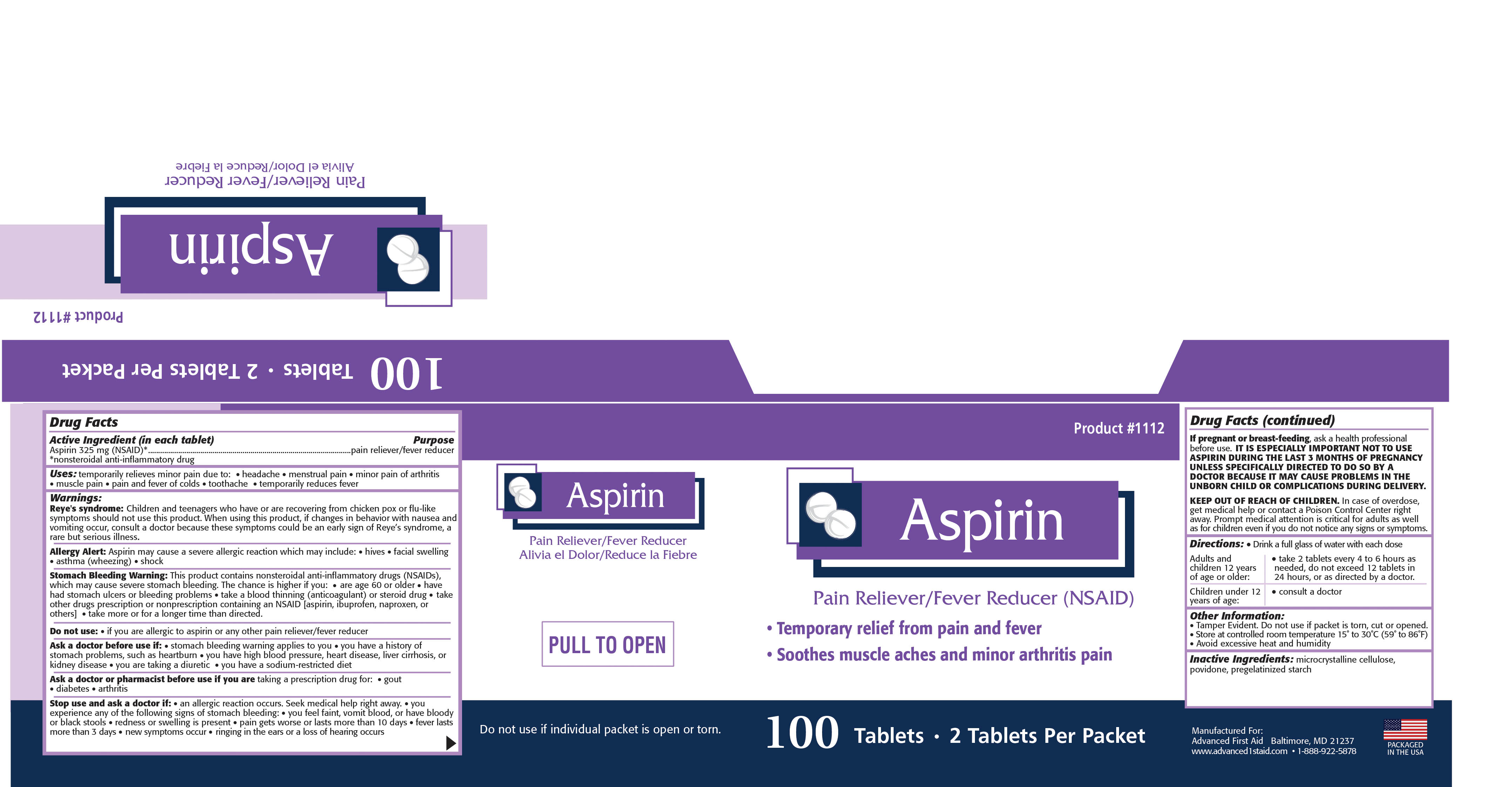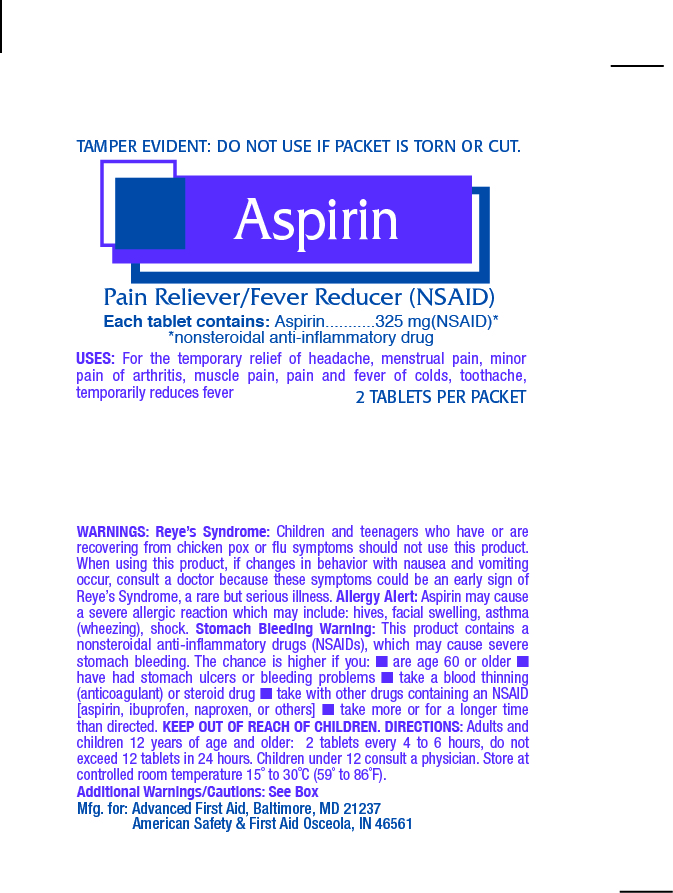 DRUG LABEL: ADVANCED ASPIRIN
NDC: 67060-232 | Form: TABLET
Manufacturer: ADVANCED FIRST AID, INC.
Category: otc | Type: HUMAN OTC DRUG LABEL
Date: 20150407

ACTIVE INGREDIENTS: ASPIRIN 325 1/1 1
INACTIVE INGREDIENTS: CELLULOSE, MICROCRYSTALLINE; POVIDONE K30; STARCH, CORN; STEARIC ACID

ACTIVE INGREDIENT IN EACH TABLET- ASPIRIN 325 MG

PURPOSE

PAIN RELIEVER/FEVER REDUCER

Uses:

temporarily relieves minor pain due to: • headache • menstrual pain • minor pain of arthritis•

muscle pain • pain and fever of colds • toothache • temporarily reduces fever

Uses:

temporarily relieves minor pain due to: • headache • menstrual pain • minor pain of arthritis

•

muscle pain • pain and fever of colds • toothache • temporarily reduces fever

Warnings:

Reye's syndrome:

Children and teenagers who have or are recovering from chicken pox or flu-like

symptoms should not use this product. When using this product, if changes in behavior with nausea and

vomiting occur, consult a doctor because these symptoms could be an early sign of Reye’s syndrome, a

rare but serious illness

.

Allergy Alert:

Aspirin may cause a severe allergic reaction which may include: • hives • facial swelling

•

asthma (wheezing) • shock

Stomach Bleeding Warning:

This product contains nonsteroidal anti-inflammatory drugs (NSAIDs),

which may cause severe stomach bleeding. The chance is higher if you:

• are age 60 or older • have

had stomach ulcers or bleeding problems

• take a blood thinning (anticoagulant) or steroid drug • take

other drugs prescription or nonprescription containing an NSAID [aspirin, ibuprofen, naproxen, or

others]

• take more or for a longer time than directed.

Do not use:

• if you are allergic to aspirin or any other pain reliever/fever reducer

Ask a doctor before use if:

• stomach bleeding warning applies to you • you have a history of

stomach problems, such as heartburn

• you have high blood pressure, heart disease, liver cirrhosis, or

kidney disease

• you are taking a diuretic • you have a sodium-restricted diet

Ask a doctor or pharmacist before use if you are

taking a prescription drug for: • gout

•

diabetes • arthritis

Stop use and ask a doctor if:

• an allergic reaction occurs. Seek medical help right away. • you

experience any of the following signs of stomach bleeding:

• you feel faint, vomit blood, or have bloody

or black stools

• redness or swelling is present • pain gets worse or lasts more than 10 days • fever lasts

more than 3 days

• new symptoms occur • ringing in the ears or a loss of hearing occurs

If pregnant or breast-feeding baby,

ask a health professional

before use. IT IS ESPECIALLY IMPORTANT NOT TO USE ASPIRIN

DURING THE LAST 3 MONTHS OF PREGNANCY UNLESS

SPECIFIC-ALLY DIRECTED TO DO SO BY A DOCTOR BECAUSE IT

MAY CAUSE PROBLEMS IN THE UNBORN CHILD OR

COMPLICATIONS DURING DELIVERY.

KEEP OUT OF REACH OF CHILDREN.

In case of overdose, get medical help or

contact a Poison Control Center right away. Prompt medical attention is critical for

adults as well as for children even if you do not notice any signs or symptoms.

Directions:

•

Drink a full glass of water with each dose

Adults and children 12 years OR OLDER :TAKE 2 TABLETS EVERY 4-6 HOURS AS needed, do not exceed 12 tablets in

24 hours, or as directed by a doctor.

Children under 12 YEARSOF AGE

• consult a doctor

Inactive Ingredients:

microcrystalline cellulose,

povidone, pregelatinized starch